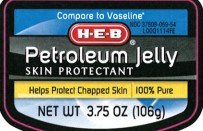 DRUG LABEL: Petroleum Skin Protectant
NDC: 37808-069 | Form: JELLY
Manufacturer: H E B
Category: otc | Type: HUMAN OTC DRUG LABEL
Date: 20260224

ACTIVE INGREDIENTS: PETROLATUM 1 g/1 g

HEB 069.001/069AA
Petroleum Jelly

Active ingredient

White petrolatum USP (100%)

Purpose

Skin protectant

Use

helps protect chapped skin

Warnings

For external use only

When using this product

- do not get into eyes

See a doctor if

condition lasts more than 7 days.

Do not use

- deep or puncture wounds
- animal bites
- serious burns

Keep out of reach of children.

If swallowed, get medical help or contact a Poison Control Center right away.

Directions

apply as needed

INACTIVE INGREDIENT

None

Dislcaimer

*This product is not manufactured or distributed by Unilever, distributor of Vaseline.

Adverse Reactions

DISTRIBUTED BY: H-E-B,

SAN ANTONIO, TX 78204

QUESTIONS? 1-888-593-0593

Principal display Panel

Compare to Vaseline*

NDC 37808-069-27

HEB

Petroleum Jelly

SKIN PROTECTANT

Helps Protect Chapped Skin

100% Pure

NET WT 3.75 OZ (106 g)